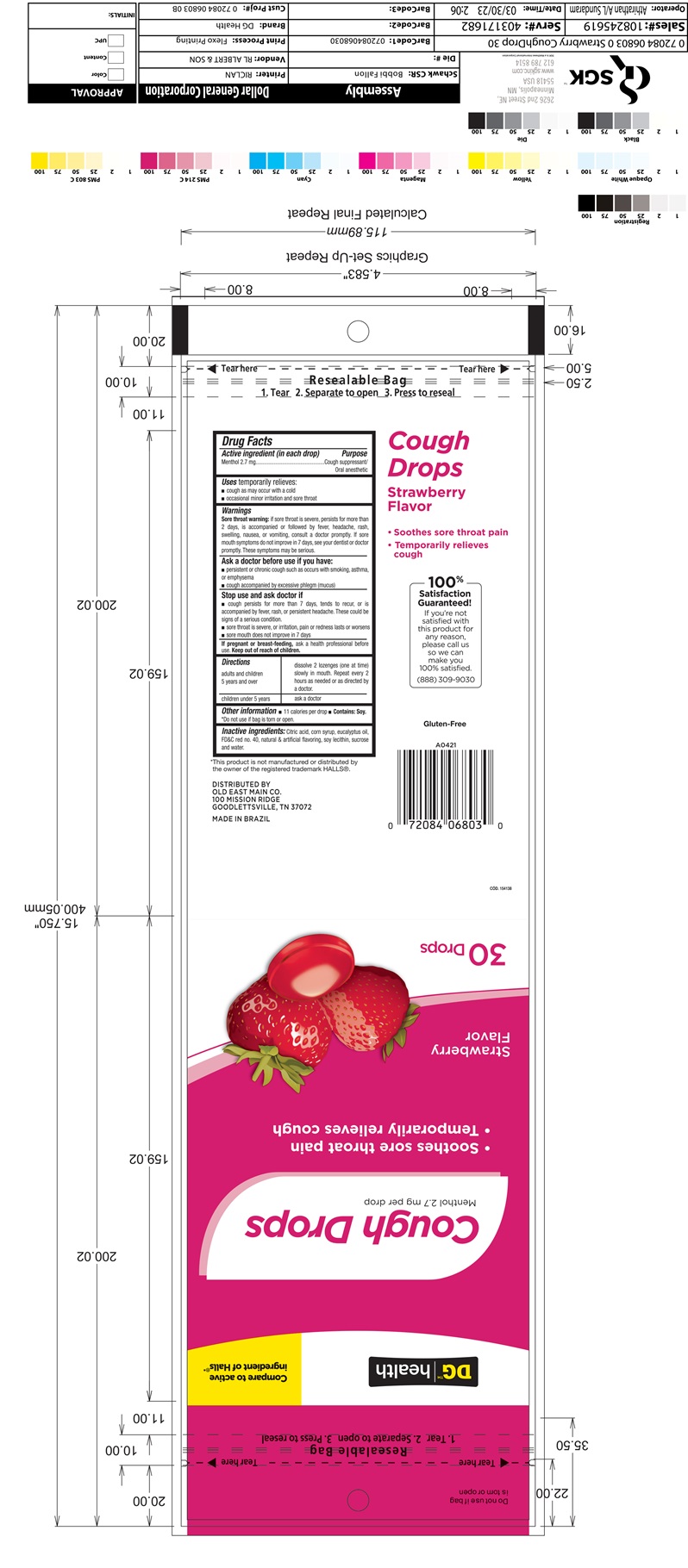 DRUG LABEL: Cough Drops Dollar General Strawberry 30ct
NDC: 75712-036 | Form: LOZENGE
Manufacturer: Dollar General Corporation
Category: otc | Type: HUMAN OTC DRUG LABEL
Date: 20251107

ACTIVE INGREDIENTS: LEVOMENTHOL 2.7 mg/1 1
INACTIVE INGREDIENTS: SUCROSE; CORN SYRUP; EUCALYPTOL; LECITHIN, SOYBEAN; FD&C RED NO. 40; CITRIC ACID MONOHYDRATE

Active ingredient (in each drop)

Menthol 2.7 mg

Purpose

Cough suppressant/Oral anesthetic

Uses

- temporarily relieves:
- cough as may occur with a cold
- occasional minor irritation and sore throat

Warnings

Sore throat warning:if sore throat is severe, persists for more than 2 days, is accompanied or followed by fever, headache, rash, swelling, nausea, or vomiting, consult a doctor promptly. If sore mouth symptoms do not improve in 7 days, see your dentist or doctor promptly. These symptoms may be serious.

Ask a doctor before use if you have:

- persistent or chronic cough such as occurs with smoking, asthma, or emphysema
- cough accompanied by excessive phlegm (mucus)

Stop use and ask a doctor if

- cough persists for more than 7 days, tends to recur, or is accompanied by fever, rash, or persistent headache, These could be signs of a serious condition.
- sore throat is severe, or irritation, pain or redness lasts or worsens
- sore mouth does not improve in 7 days

If pregnant or breast-feeding
ask a health professional before use.

Directions

adults and children 5 years and over | dissolve 2 lozenge (one at time) slowly in mouth. Repeat every 2 hours as needed or as directed by a doctor.
children under 5 years | ask a doctor

Other information

- 11 calories per drop
- do not use if bags is torn or open
- Contains: Soy

Inactive ingredients

Citric Acid, corn syrup, eucalyptus oil, FD&C red no. 40, natural & artificial flavoring, soy lecithin, sucrose and water.